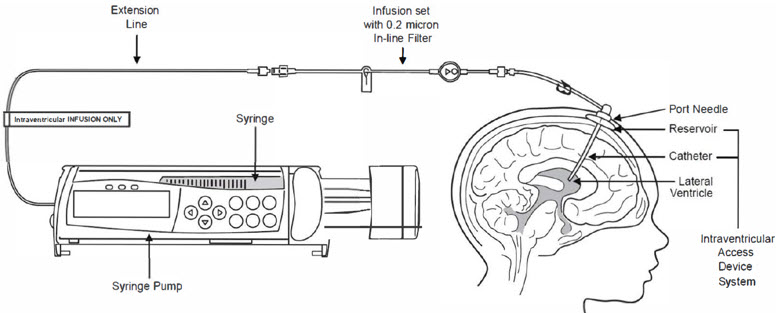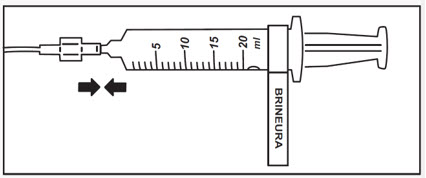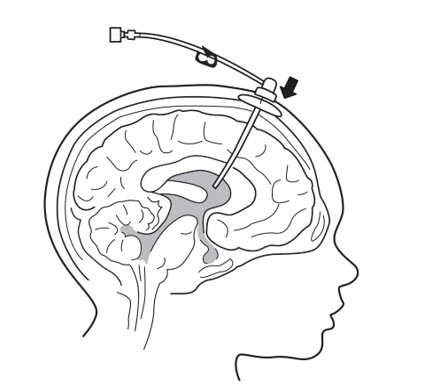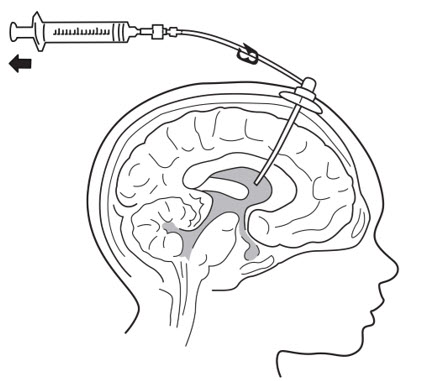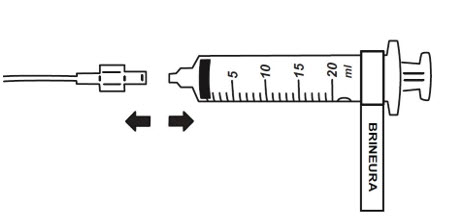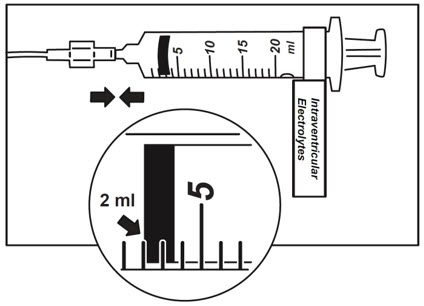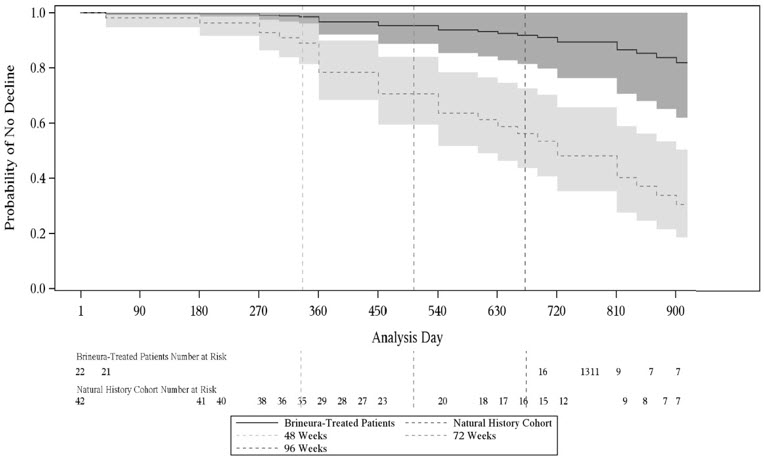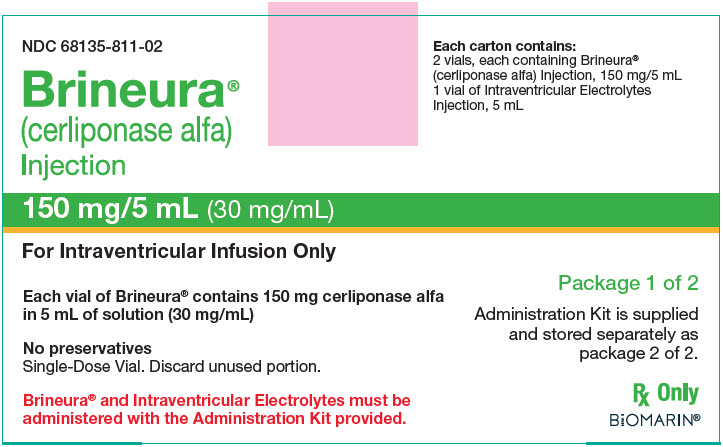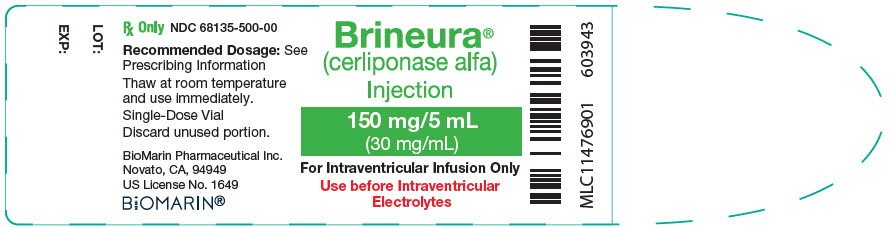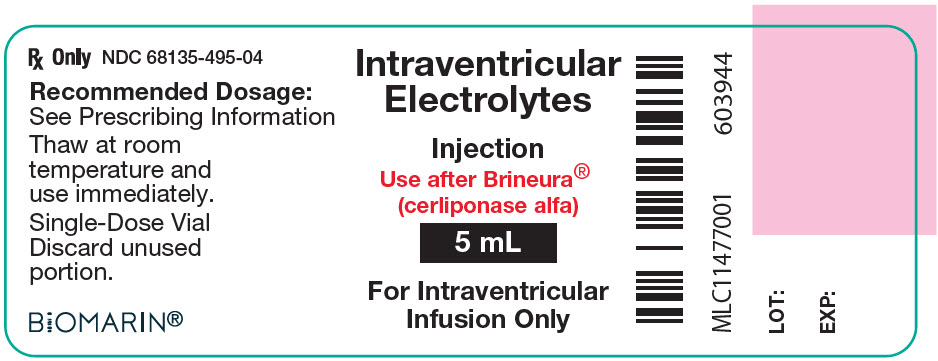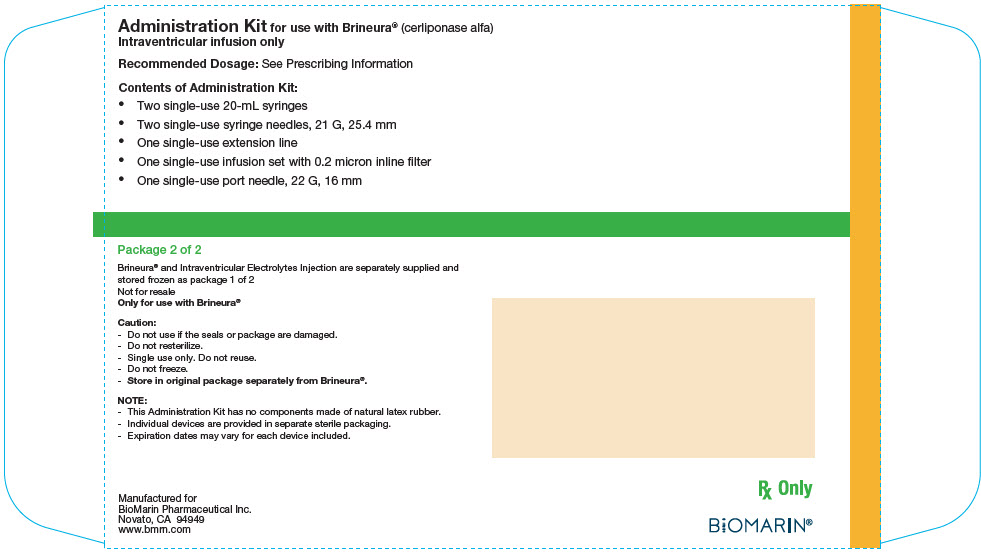 DRUG LABEL: Brineura
NDC: 68135-811 | Form: KIT | Route: INTRAVENTRICULAR
Manufacturer: BioMarin Pharmaceutical Inc.
Category: prescription | Type: HUMAN PRESCRIPTION DRUG LABEL
Date: 20240805

ACTIVE INGREDIENTS: CERLIPONASE ALFA 150 mg/5 mL

HIGHLIGHTS OF PRESCRIBING INFORMATION

These highlights do not include all the information needed to use BRINEURA safely and effectively. See full prescribing information for BRINEURA.
BRINEURA (cerliponase alfa) injection, for intraventricular use
Initial U.S. Approval: 2017

WARNING: HYPERSENSITIVITY REACTIONS INCLUDING ANAPHYLAXIS

See full prescribing information for complete boxed warning

- Anaphylaxis has occurred during the early course of enzyme replacement therapy and after extended duration of therapy. (5.1)
- Initiate BRINEURA in a healthcare setting with appropriate medical monitoring and support measures, including access to cardiopulmonary resuscitation equipment. (5.1)
- If a severe hypersensitivity reaction (e.g., anaphylaxis) occurs, discontinue BRINEURA and immediately initiate appropriate medical treatment, including use of epinephrine. (5.1)

RECENT MAJOR CHANGES

Boxed Warning | 7/2024
Indication and Usage (1) | 7/2024
Dosage and Administration (2.1, 2.2, 2.3, 2.6) | 7/2024
Warnings and Precautions (5.1, 5.5) | 7/2024

1 INDICATIONS AND USAGE

BRINEURA is a hydrolytic lysosomal N-terminal tripeptidyl peptidase indicated to slow the loss of ambulation in pediatric patients with neuronal ceroid lipofuscinosis type 2 (CLN2 disease), also known as tripeptidyl peptidase 1 (TPP1) deficiency. (1)

2 DOSAGE AND ADMINISTRATION

- Administration of BRINEURA should be supervised by a healthcare provider knowledgeable in the management of hypersensitivity reactions including anaphylaxis. (2.1)
- BRINEURA should be administered by or under the supervision of a physician experienced in intraventricular administration. (2.1)
- Premedication of patients with antihistamines with or without antipyretics or corticosteroids is recommended. (2.1)
- Prior to each infusion, inspect the scalp for signs of intraventricular access device reservoir leakage, failure, or potential infection. (2.1)
- Recommended BRINEURA dosage is 300 mg administered once every other week as an intraventricular infusion. In patients less than 2 years of age, lower doses are recommended. (2.2)
- Dosing is not recommended in patients less than 37 weeks post-menstrual age or those weighing less than 2.5 kg. (2.2)
- See the full prescribing information for dosage modifications due to hypersensitivity reactions. (2.3)
- See the full prescribing information for preparation and administration instructions. (2.4, 2.6)

3 DOSAGE FORMS AND STRENGTHS

Injection: BRINEURA 150 mg/5 mL (30 mg/mL) solution, two single-dose vials per carton co-packaged with Intraventricular Electrolytes Injection 5 mL in a single-dose vial. (3)

4 CONTRAINDICATIONS

- Any sign or symptom of acute or unresolved localized infection on or around the device insertion site (e.g. cellulitis or abscess); or suspected or confirmed CNS infection (e.g., cloudy CSF or positive CSF gram stain, or meningitis). (4)
- Any acute intraventricular access device-related complication (e.g., leakage, extravasation of fluid, or device failure). (4)
- Patients with ventriculoperitoneal shunts. (4)

5 WARNINGS AND PRECAUTIONS

- Meningitis and Other Intraventricular Access Device-Related Infections: Monitor the device insertion site for signs of infection. (4, 5.2)
- Intraventricular Access Device-Related Complications: Consult a neurosurgeon for any complications with the implanted device. In case of device-related complication, discontinue the infusion and refer to the device labeling for further instructions. (4, 5.3)
- Cardiovascular Adverse Reactions: Monitor vital signs before, during, and post-infusion. Monitor Electrocardiogram (ECG) in patients with a history of bradycardia, conduction disorder, or with structural heart disease, during the infusion. In patients without cardiac abnormalities, perform regular 12-lead ECG evaluations every 6 months. (2.5, 5.4)
- Infusion-Associated Reactions (IARs): If an IAR occurs, decreasing the infusion rate, temporarily stopping the infusion, and/or administering antihistamines and/or antipyretics may ameliorate the symptoms. (5.5)

6 ADVERSE REACTIONS

Most common adverse reactions (≥8%) are: pyrexia, ECG abnormalities, decreased CSF protein, vomiting, seizures, device-related complications, hypersensitivity, increased CSF protein, hematoma, headache, irritability, pleocytosis, device-related infections, bradycardia, feeling jittery, and hypotension. (6.1)

To report SUSPECTED ADVERSE REACTIONS, contact BioMarin at 1-866-906-6100 or FDA at 1-800-FDA-1088 or www.fda.gov/medwatch.

FULL PRESCRIBING INFORMATION

WARNING: HYPERSENSITIVITY REACTIONS INCLUDING ANAPHYLAXIS

Patients treated with enzyme replacement therapies have experienced life-threatening hypersensitivity reactions, including anaphylaxis. Anaphylaxis has occurred during the early course of enzyme replacement therapy and after extended duration of therapy.

Initiate BRINEURA in a healthcare setting with appropriate medical monitoring and support measures, including access to cardiopulmonary resuscitation equipment. If a severe hypersensitivity reaction (e.g., anaphylaxis) occurs, discontinue BRINEURA and immediately initiate appropriate medical treatment, including use of epinephrine. Inform patients of the symptoms of life-threatening hypersensitivity reactions, including anaphylaxis and to seek immediate medical care should symptoms occur [see Warnings and Precautions (5.1)].

1 INDICATIONS AND USAGE

BRINEURA is indicated to slow the loss of ambulation in pediatric patients with neuronal ceroid lipofuscinosis type 2 (CLN2 disease), also known as tripeptidyl peptidase 1 (TPP1) deficiency.

2 DOSAGE AND ADMINISTRATION

2.1 Recommendations Prior to BRINEURA Treatment

- Administration of BRINEURA should be supervised by a healthcare provider knowledgeable in the management of hypersensitivity reactions including anaphylaxis.
- Initiate BRINEURA in a healthcare setting with appropriate medical monitoring and support measures, including access to cardiopulmonary resuscitation equipment [see Warnings and Precautions (5.1)].
- BRINEURA should be administered by or under the supervision of a physician experienced in intraventricular administration via a surgically implanted intraventricular access device system which consists of the reservoir and catheter components [see Dosage and Administration (2.6)].
- Premedication of patients with antihistamines with or without antipyretics or corticosteroids is recommended 30 to 60 minutes prior to the start of infusion [see Warnings and Precautions (5.1, 5.5)].
- Aseptic technique must be strictly observed during preparation and administration [see Dosage and Administration (2.6)].
- Prior to each infusion of BRINEURA, inspect the scalp for signs of intraventricular access device reservoir leakage, failure or potential infection [see Warnings and Precautions (5.2, 5.3)].
- Prior to each infusion of BRINEURA and when clinically indicated, obtain a sample of CSF for cell count and culture [see Warnings and Precautions (5.2)].
- Replace the intraventricular access device reservoir prior to 4 years of single-puncture administrations [see Warnings and Precautions (5.3)].

2.2 Recommended Dosage and Administration

The recommended dosage of BRINEURA in pediatric patients is provided in Table 1. The dose is administered once every other week by intraventricular infusion.

BRINEURA is not recommended in patients less than 37 weeks post-menstrual age (gestational age at birth plus post-natal age) or those weighing less than 2.5 kg [see Use in Specific Populations (8.4)].

Administer BRINEURA first followed by infusion of the Intraventricular Electrolytes. The complete BRINEURA infusion, including the required infusion of Intraventricular Electrolytes, is approximately 2 to 4.5 hours, depending on the dose and volume administered. See Table 1 for the appropriate volume and infusion rate. For volumes that are not whole numbers, see Dosage and Administration (2.6).

Table 1: BRINEURA Dose, Volume, and Infusion Rate by Age
Age groups | BRINEURA dose administered every other week | Volume of BRINEURA solution | Infusion rate
Birth to < 6 months | 100 mg | 3.3 mL | 1.25 mL/hr
6 months to < 1 year | 150 mg | 5 mL | 2.5 mL/hr
1 year to < 2 years | 200 mg (first 4 doses) | 6.7 mL (first 4 doses) | 2.5 mL/hr
 | 300 mg (subsequent doses) | 10 mL (subsequent doses)
2 years and older | 300 mg | 10 mL | 2.5 mL/hr

Missed Dose

If one or more doses are missed, restart BRINEURA treatment as soon as possible, maintaining the 2-week interval between infusions thereafter.

2.3 Administration Modifications due to Hypersensitivity Reactions Including Anaphylaxis

In the event of a severe hypersensitivity reaction (e.g., anaphylaxis), immediately discontinue BRINEURA administration and initiate appropriate medical treatment. If the decision is made to readminister BRINEURA after the occurrence of anaphylaxis, initiate the subsequent infusion at approximately one-half the infusion rate at which the anaphylactic reaction occurred with appropriate premedication. For additional recommendations in the event of a hypersensitivity reaction, see Warnings and Precautions (5.1).

2.4 Preparation Instructions for Intraventricular Administration of the Product

BRINEURA and the Intraventricular Electrolytes must only be administered by the intraventricular route, using the provided Administration Kit for use with BRINEURA. Each vial of BRINEURA and Intraventricular Electrolytes is intended for a single dose only.

BRINEURA is administered into the cerebrospinal fluid (CSF) by infusion via a surgically implanted reservoir and catheter (the "intraventricular access device system"). BRINEURA is intended to be administered via the Codman® HOLTER RICKHAM Reservoirs (Part Numbers: 82-1625, 82-1621, 82-1616) with the Codman® Ventricular Catheter (Part Number: 82-1650). The intraventricular access device reservoir and catheter must be implanted prior to the first infusion. It is recommended that the first dose be administered at least 5 to 7 days after device implantation.

BRINEURA is intended to be administered with the B Braun Perfusor® Space Infusion Pump System (Product Code: 8713030U). If an alternative pump must be used, the essential performance requirements for this syringe pump used to deliver BRINEURA are as follows:

- Delivery rate of 1.25 or 2.5 mL per hr with delivery accuracy of +/- 1 mL per hr
- Compatible with 20 mL syringes provided in the Administration Kit for use with BRINEURA
- Occlusion alarm setting to ≤ 281 mm Hg
- Cleared for intraventricular route of administration

Administer BRINEURA and the Intraventricular Electrolytes using the provided Administration Kit for use with BRINEURA components [see How Supplied/Storage and Handling (16)].

Each infusion consists of 3.3 to 10 mL of BRINEURA followed by 2 mL of Intraventricular Electrolytes. The complete infusion must be administered using an infusion set with a 0.2 micron inline filter. The Intraventricular Electrolytes are used to flush the infusion line, port needle, and intraventricular access device in order to fully administer BRINEURA and to maintain patency of the intraventricular access device.

Supplies for Infusion Preparation

- BRINEURA and Intraventricular Electrolytes Injection vials (package 1 of 2) [see How Supplied/Storage and Handling (16)]
- Administration Kit for use with BRINEURA (package 2 of 2) [see How Supplied/Storage and Handling (16)]
- Syringe pump (not supplied)
- Empty sterile single-use luer lock syringe, no larger than 3 mL (not supplied)

Inspect the Administration Kit infusion components to ensure the components are in the individual packages and have not been compromised.

Thaw BRINEURA and Intraventricular Electrolytes Injection vials at room temperature 20°C to 25°C (68°F to 77°F) for approximately 60 minutes. Do not thaw or warm vials any other way. Do not shake vials. Condensation will occur during thawing period. Do not re-freeze vials or freeze syringes containing BRINEURA or Intraventricular Electrolytes.

Inspect fully thawed BRINEURA and Intraventricular Electrolytes Injection vials. Parenteral drug products should be inspected visually for particulate matter and discoloration prior to administration, whenever solution and container permit. BRINEURA is a clear to slightly opalescent and colorless to pale yellow solution. Intraventricular Electrolytes is a clear to colorless solution. Do not use if the solutions are discolored or if there is other foreign particulate matter in the solutions. BRINEURA vials may occasionally contain thin translucent fibers or opaque particles. These naturally occurring particles are cerliponase alfa. These particles are removed via the 0.2 micron inline filter without having a detectable effect on the purity or strength of BRINEURA. Intraventricular Electrolytes may contain particles, which appear during the thaw period; however, these dissolve when the solution reaches room temperature.

2.5 Storage Instructions for the Thawed Product and Product in Syringe

Storage of Thawed Product

Use thawed BRINEURA and Intraventricular Electrolytes immediately. If thawed BRINEURA and Intraventricular Electrolytes is not used immediately, store in the refrigerator at 2°C to 8°C (36°F to 46°F) for no more than 24 hours. Discard the thawed product after 24 hours if refrigerated.

Storage of Product in Syringe

Use product held in labeled syringes immediately. If product held in labeled syringe is not used immediately, store in the refrigerator at 2°C to 8°C (36°F to 46°F) for no more than 4 hours prior to infusion. Discard the product held in labeled syringe after 4 hours if refrigerated.

2.6 Administration Instructions for Intraventricular Infusion

Intraventricular Infusion of BRINEURA

Figure 1 represents the intraventricular infusion system set up. Use aseptic technique during the infusion.
Follow the steps below to proceed with the intraventricular infusion.

Figure 1

1. Use aseptic technique when preparing the BRINEURA syringe for infusion. Label one sterile syringe "BRINEURA" and attach the syringe needle.
2. Confirm required dose and volume based on patient age per Table 1. Remove the green flip-off caps from one or both BRINEURA vials. Each BRINEURA vial contains 150 mg or 5 mL. Use the "BRINEURA" labeled syringe to withdraw the volume of BRINEURA solution from the vial per the required dose (see Table 1). Intermediate volumes that fall between 1 mL increments should be drawn up in the syringe to the nearest whole number, specifically 3.3 mL to 4 mL and 6.7 mL to 7 mL. Do not dilute BRINEURA. Do not mix BRINEURA with any other drug.
  Discard any unused portion left in the vial.
3. Label the infusion line "intraventricular infusion only" (see Figure 1).
4. Attach the syringe containing BRINEURA to the extension line (see Figure 2). Then connect the extension line to the infusion set with a 0.2 micron inline filter (see Figure 1).
  Figure 2
5. Prime the infusion components with BRINEURA.
6. Inspect scalp for signs of intraventricular access device reservoir leakage or failure and for potential infections [see Warnings and Precautions (5.2, 5.3)].
7. Prepare the scalp for intraventricular infusion per institution standard of care.
8. Insert port needle into intraventricular access device reservoir (see Figure 3).
  Figure 3
9. Connect a separate empty sterile single-use luer lock syringe, no larger than 3 mL (not provided) to the port needle. Withdraw 0.5 mL to 1 mL of CSF to check patency of intraventricular access device (see Figure 4) and send specimen for culture.
  - Do not return CSF to intraventricular access device.
  - Routinely send CSF samples for infection monitoring [see Warnings and Precautions (5.2)].
  Figure 4
10. Attach the infusion set with 0.2 micron inline filter to the port needle (see Figure 1).
  - Secure the components per institution standard of care.
11. Place the syringe containing BRINEURA into the syringe pump and program the pump to deliver at an infusion rate of 1.25 or 2.5 mL per hour (Table 1). Set the pump volume limit to deliver the exact volume that corresponds to the dose of BRINEURA solution appropriate for the patient's age (Table 1). Set the occlusion alarm setting to alert at pressure ≤ 281 mm Hg. See syringe pump operating manual for details. Do not deliver as a bolus or manually.
12. Administer pre-medication 30 to 60 minutes prior to the start of infusion.
13. Monitor vital signs (blood pressure, heart rate) prior to the start of infusion, periodically during infusion, and post-infusion [see Warnings and Precautions (5.4)].
14. Initiate infusion of BRINEURA at a rate of 1.25 or 2.5 mL per hour (Table 1).
15. Periodically inspect the infusion system during the infusion for signs of leakage or delivery failure [see Warnings and Precautions (5.3)].
16. When the BRINEURA infusion is complete, detach and remove the syringe from the pump and disconnect from the tubing (see Figure 5). Discard the syringe containing any residual drug. Proceed to Step 16 for Intraventricular Electrolytes infusion.
  Figure 5

Intraventricular Infusion of Intraventricular Electrolytes

Administer the Intraventricular Electrolytes provided after BRINEURA infusion is complete.

17. Use aseptic technique when preparing the Intraventricular Electrolytes syringe for infusion. Label one sterile syringe "Intraventricular Electrolytes" and attach the syringe needle. Remove the yellow flip-off cap from the Intraventricular Electrolytes Injection vial. Withdraw 2 mL of Intraventricular Electrolytes. Discard the remaining unused portion.
18. Attach the syringe to the extension line (see Figure 6).
  Figure 6
19. Place the syringe containing Intraventricular Electrolytes into the syringe pump and program pump to deliver at an infusion rate of 1.25 or 2.5 mL per hour (Table 1). Set the pump volume limit to deliver 2 mL. Set the occlusion alarm setting to alert at pressure ≤ 281 mm Hg. See syringe pump operating manual for details. Do not deliver as a bolus or manually.
20. Initiate infusion of Intraventricular Electrolytes at a rate of 2.5 mL per hour.
21. Periodically inspect the infusion system during the infusion for signs of leakage or delivery failure.
22. When the Intraventricular Electrolytes infusion is complete, detach and remove the empty syringe from the pump and disconnect from the infusion line.
23. Remove the port needle. Apply gentle pressure and bandage the infusion site per institution standard of care.

Dispose of the infusion components, needles, unused solutions and other waste materials in accordance with local requirements.

3 DOSAGE FORMS AND STRENGTHS

Injection: BRINEURA 150 mg/5 mL (30 mg/mL) solution, two single-dose vials per carton co-packaged with Intraventricular Electrolytes Injection 5 mL in a single-dose vial. BRINEURA is a clear to slightly opalescent and colorless to pale yellow solution. Intraventricular Electrolytes is a clear to colorless solution [see How Supplied/Storage and Handling (16)].

4 CONTRAINDICATIONS

BRINEURA is contraindicated in patients with:

- any sign or symptom of acute, unresolved localized infection on or around the device insertion site (e.g., cellulitis or abscess); or suspected or confirmed CNS infection (e.g., cloudy CSF or positive CSF gram stain, or meningitis) [see Warnings and Precautions (5.2)].
- any acute intraventricular access device-related complication (e.g., leakage, extravasation of fluid, or device failure) [see Warnings and Precautions (5.3)].
- ventriculoperitoneal shunts.

5 WARNINGS AND PRECAUTIONS

5.1 Hypersensitivity Reactions Including Anaphylaxis

Life-threatening hypersensitivity reactions including anaphylaxis have been reported in patients treated with enzyme replacement therapies, including BRINEURA. BRINEURA-treated patients have had these reactions occur in clinical studies and postmarketing use [see Adverse Reactions (6)]. In clinical Trial 1 and Trial 2 to 96 weeks, a total of 11 of 24 (46%) patients experienced hypersensitivity reactions during the infusion or within 24 hours of completion of the infusion. Patients in clinical trials were routinely pre-medicated with antihistamines with or without antipyretics or corticosteroids, prior to infusion of BRINEURA. During postmarketing use, anaphylactic reactions occurred during or within several hours of BRINEURA infusion. Epinephrine was administered in these patients, and they received subsequent BRINEURA infusions without recurrence of anaphylaxis.

In Trial 3, hypersensitivity reactions were reported in 5 of 8 (63 %) patients less than 3 years of age at baseline as compared to 0 of 6 patients ≥ 3 years of age at baseline [see Adverse Reactions (6.1)]. Of the reported hypersensitivity reactions, a single anaphylactic reaction occurred in a subject < 3 years of age.

Anaphylaxis has occurred during the early course of enzyme replacement therapy and after extended duration of therapy. Administration of BRINEURA should be supervised by a healthcare provider knowledgeable in the management of hypersensitivity reactions including anaphylaxis. Initiate BRINERUA in a healthcare setting with appropriate medical monitoring and support measures, including access to cardiopulmonary resuscitation equipment. Premedication of patients with antihistamines with or without antipyretics or corticosteroids is recommended 30 to 60 minutes prior to the start of infusion. Observe patients closely during and after the infusion. If a severe hypersensitivity reaction (e.g., anaphylaxis) occurs, discontinue BRINEURA and immediately initiate appropriate medical treatment including use of epinephrine. Inform patients and caregivers of the symptoms of life-threatening hypersensitivity reactions, including anaphylaxis and to seek immediate medical care should symptoms occur.

The management of hypersensitivity reactions should be based on the severity of the reaction and may include temporarily interrupting the infusion, and/or treatment with antihistamines, antipyretics, and/or corticosteroids. Consider the risks and benefits of readministration of BRINEURA following an anaphylactic reaction. If the decision is made to readminister BRINEURA after the occurrence of anaphylaxis, ensure appropriately trained personnel and equipment for emergency resuscitation (including epinephrine and other emergency medicines) are readily available during infusion. Initiate subsequent infusion at approximately one-half the initial infusion rate at which the anaphylactic reaction occurred.

5.2 Meningitis and Other Intraventricular Access Device-Related Infections

Bacterial meningitis requiring antibiotic treatment and removal of the device was reported during postmarketing use of BRINEURA. Additionally, in clinical trials and during postmarketing use there were reports of other device-related clinical infections which were confirmed by positive CSF cultures, treated with antibiotics and removal of the entire intraventricular access device, and in which patients resumed treatment with BRINEURA after the device was replaced [see Adverse Reactions (6.1)]. In all cases, antibiotics were administered, the intraventricular access devices were removed and replaced, and patients resumed treatment with BRINEURA.

The signs and symptoms of infections may not be readily apparent in patients with CLN2 disease. To reduce the risk of infectious complications, BRINEURA should be administered by, or under the supervision of, a physician experienced in intraventricular administration. Prior to each infusion of BRINEURA and when clinically indicated, obtain a sample of CSF for cell count and culture. Do not administer BRINEURA if there are localized signs of infection on or around the device insertion site, such as erythema, tenderness, or discharge or suspected or confirmed CNS infection (e.g., cloudy CSF or positive CSF gram stain, or meningitis) [see Contraindications (4)].

Healthcare providers should be vigilant for the development of signs and symptoms of infection, including meningitis, during treatment with BRINEURA and monitor the device insertion site for signs of infection.

5.3 Intraventricular Access Device-Related Complications

During the clinical trials and in postmarketing reports, intraventricular access device-related complications were reported (e.g., device leakage, device failure extravasation of CSF fluid, or bulging of the scalp around or above the intraventricular access device) [see Adverse Reactions (6.1)]. For any complications with the implanted intraventricular access device, consult with a neurosurgeon to confirm the integrity or performance of the device. In case of intraventricular access device-related complications, discontinue the BRINEURA infusion and refer to the device manufacturer's labeling for further instructions [see Contraindications (4)].

Material degradation of the intraventricular access device reservoir was reported after approximately 4 years of administration, which may impact the effective and safe use of the device. During benchtop testing such material degradation was recognized after approximately 105 perforations of the intraventricular access device. The intraventricular access device should be replaced prior to 4 years of single-puncture administrations, which equates to approximately 105 administrations of BRINEURA.

5.4 Cardiovascular Adverse Reactions

Monitor vital signs (blood pressure, heart rate) before infusion starts, periodically during infusion, and post-infusion in a healthcare setting [see Dosage and Administration (2.6)]. Upon completion of the infusion, clinically assess the patient status. Continued observation may be necessary if clinically indicated.

Perform electrocardiogram (ECG) monitoring during infusion in patients with a history of bradycardia, conduction disorder, or with structural heart disease, as some patients with CLN2 disease may develop conduction disorders or heart disease. In patients without cardiac abnormalities, regular 12-lead ECG evaluations should be performed every 6 months.

In clinical Trial 1 and Trial 2 to 96 weeks, hypotension was reported in 2 of 24 (8%) patients, which occurred during or up to eight hours after BRINEURA infusion. Patients did not require alteration in treatment, and reactions resolved spontaneously or after intravenous fluid administration [see Adverse Reactions (6.1)].

5.5 Infusion-Associated Reactions

Infusion-associated reactions (IARs) such as vomiting, seizure, rash, pyrexia, hypersensitivity, and anaphylactic reaction have been observed in patients treated with BRINEURA [see Adverse Reactions (6.1)].

Premedication of patients with antihistamines with or without antipyretics or corticosteroids is recommended 30 to 60 minutes prior to the start of infusion. If an IAR occurs, decreasing the infusion rate, temporarily stopping the infusion, and/or administering antihistamines and/or antipyretics may ameliorate the symptoms. Closely monitor patients who have experienced IARs when re-administering BRINEURA.

In Trial 3, infusion-associated reactions were reported in 8 of 8 patients less than 3 years of age at baseline as compared to 4 of 6 patients ≥ 3 years of age at baseline.

6 ADVERSE REACTIONS

The following adverse reactions are described below and elsewhere in the labeling:

- Hypersensitivity Reactions Including Anaphylaxis [see Warnings and Precautions (5.1)]
- Meningitis and Other Intraventricular Access Device-Related Infections [see Warnings and Precautions (5.2)]
- Intraventricular Access Device-Related Complications [see Warnings and Precautions (5.3)]
- Cardiovascular Adverse Reactions [see Warnings and Precautions (5.4)]
- Infusion-Associated Reactions [see Warnings and Precautions (5.5)]

6.1 Clinical Trials Experience

Because clinical trials are conducted under widely varying conditions, adverse reaction rates observed in the clinical trials of a drug cannot be directly compared to rates in the clinical trials of another drug and may not reflect the rates observed in practice.

Trial 1 and Trial 2

The safety of BRINEURA was evaluated in 24 patients with CLN2 disease who received at least one 300 mg dose of BRINEURA given by intraventricular infusion in a clinical trial with extension (Trials 1 and 2) of up to 161 weeks [see Clinical Studies (14)]. Table 2 summarizes the most common adverse reactions that occurred in BRINEURA-treated patients through 96 weeks.

Table 2: Adverse Reactions Reported in ≥ 8% of Symptomatic Pediatric Patients with CLN2 Disease in BRINEURA Trial 1 and Trial 2 at Week 96
Adverse Reaction | Patients Treated with BRINEURA n=24 (%)
Increased body temperature [Increased body temperature includes: increased body temperature and pyrexia] | 17 (71)
ECG abnormalities [ECG abnormalities include: non-specific repolarization abnormality, notched QRS, ST segment elevation, biphasic T wave abnormality, supraventricular extrasystoles, bradycardia, sinus tachycardia, and intraventricular conduction delay] | 17 (71)
Decreased CSF protein | 17 (71)
Vomiting | 15 (63)
Seizures [Seizures include: atonic, generalized tonic-clonic, focal, and absence] | 12 (50)
Device-related complications [Device-related complications include device-related infection, delivery system-related complications (needle issues, device leakage, device malfunction, device difficult to use, medical device site irritation, device breakage, etc.) and pleocytosis.] | 12 (50)
Hypersensitivity [Hypersensitivity includes only hypersensitivity [see Warnings and Precautions (5.4)]] | 9 (38)
Increased CSF protein | 5 (21)
Hematoma | 5 (21)
Headache | 4 (17)
Irritability | 4 (17)
Pleocytosis | 4 (17)
Device-related infections [Device-related infections include: Propionibacterium acnes and Staphylococcus epidermidis] | 2 (8)
Bradycardia | 2 (8)
Feeling jittery | 2 (8)
Hypotension | 2 (8)

Description of Selected Adverse Reactions from Trial 1 and Trial 2 at 96 weeks

Seizures

Seizures were reported in 12 of 24 (50%) patients. The seizure types reported include atonic, generalized tonic-clonic, focal, and absence. Seizures were managed with standard anti-convulsive therapies and did not result in discontinuation of BRINEURA treatment.

Device-Related Complications

Adverse reactions related to the device were observed in 12 of 24 (50%) of patients. Device-related adverse reactions include infection, delivery system-related complications, and pleocytosis. Nine out of 24 patients (38%) experienced adverse reactions, which involved complications of the non-implanted delivery system components. Four out of 24 patients (16%) had device-related adverse reactions, which required medical intervention, including two patients (8%) with intraventricular access device-related CNS infections, and one patient (4%) each with leakage of the intraventricular access device and pleocytosis. Device-related infections were diagnosed by increased CSF pleocytosis and microbiology culture and organism identification, without accompanying signs and symptoms of meningitis. Intraventricular access devices were replaced and infections were treated with antibiotics. Device-related complications did not result in discontinuation of BRINEURA treatment.

Hematoma

Hematoma adverse reactions were reported in 5 of 24 (21%) patients treated with BRINEURA and presented as hematoma, post procedural hematoma, traumatic hematoma and subdural hematoma. Hematomas did not require treatment and did not interfere with BRINEURA infusion.

Hypersensitivity

Hypersensitivity reactions were reported in 11 out of 24 patients (46%) treated with BRINEURA during or within 24 hours after completion of the BRINEURA infusion, despite pre-medication with antihistamines with or without antipyretics or corticosteroids. The most common manifestations observed concomitantly with hypersensitivity included pyrexia with vomiting, pleocytosis, or irritability, which are not consistent with classic immune mediated hypersensitivity. Symptoms resolved over time or with administration of antipyretics, antihistamines and/or corticosteroids and no patient discontinued treatment with BRINEURA.

One patient experienced hypoxia (decreased oxygen saturation less than 88% by pulse oximeter), 8 hours after BRINEURA infusion, followed by a low mean arterial pressure at 15 hours post infusion. Symptoms resolved after oxygen administration, airway repositioning and normal saline infusion. One patient reported decreased oxygen saturation (90% by pulse oximeter), 45 minutes after starting BRINEURA with associated low diastolic blood pressures. Hypoxia resolved after oxygen administration. No treatment was administered for the low diastolic blood pressure, which returned to normal while the patient continued to receive BRINEURA infusion without change to the infusion rate or dose.

Trial 3

Trial 3 enrolled 14 patients aged 1 to 6 years at baseline who received BRINEURA at the recommended dose based on the age of the patient, every other week for a median of 142 weeks. Adverse reactions that occurred in at least 5% of patients are described in Table 3.

The most frequent adverse reactions reported in patients < 3 years treated with BRINEURA were similar to those observed in patients ≥ 3 years of age except for hypersensitivity reactions, which were reported in 5 of 8 (63%) in patients < 3 years at baseline compared with 0 of 6 in patients ≥ 3 years of age at baseline. The most common manifestations of hypersensitivity were pyrexia and vomiting and the timing and resolution were similar to Trials 1 and 2. Symptoms of severe hypersensitivity reactions (e.g., anaphylaxis) included tachycardia, bronchospasm, rash, diarrhea, hypotension, increased body temperature and vomiting.

Drug-related IARs

In Trial 3, 12 patients (86%) who received BRINEURA had 83 IARs. Of those, 8 patients were < 3 years of age and 4 were ≥ 3 years of age. The symptoms occurring in more than one patient consisted of vomiting, seizure, rash, pyrexia, hypersensitivity, and abnormal electrocardiogram. Eight (57%) patients had serious IARs: pyrexia, hypersensitivity, anaphylactic reaction, seizure, and pleocytosis.

Device-related IARs

In Trial 3, 3 patients (21%) who received BRINEURA had 3 IARs related to the intraventricular device. Of those, 2 were < 3 years of age and 1 was ≥ 3 years of age. The events were: device leakage, device breakage, and CSF red blood cell count positive. One (7%) patient had a serious IAR of device leakage.

Table 3: Adverse Reactions Reported in ≥ 5% of Pediatric Patients (1 to 6 years of age) with CLN2 Disease treated with BRINEURA in Trial 3
Adverse Reaction | Age 1 to 3 years n=8 (%) | Age 3 to 6 years n=6 (%) | Total n=14 (%)
ECG abnormalities [ECG abnormalities include: non-specific repolarization abnormality, supraventricular extrasystoles, possible left ventricular hypertrophy, intermittent 2nd degree AV Block (type 2 Mobitz), incomplete right bundle branch block, and prominent Q wave.] | 8 (100) | 6 (100) | 14 (100)
Decreased CSF protein | 8 (100) | 4 (67) | 12 (86)
Increased body temperature [Increased body temperature includes: increased body temperature and pyrexia.] | 6 (75) | 6 (100) | 12 (86)
Seizures [Seizures include: atonic, febrile convulsion, generalized tonic-clonic, partial, partial with secondary generalization, petit mal epilepsy, myoclonic and status epilepticus.] | 4 (50) | 4 (67) | 8 (57)
Device-related complications [Device-related complications include device-related infection, delivery system-related complications (needle issues, device leakage, device malfunction, device difficult to use, medical device site irritation, device breakage, etc.)] | 3 (36) | 2 (33) | 5 (36)
Vomiting | 2 (25) | 3 (50) | 5 (36)
Hypersensitivity [Hypersensitivity includes only the term of hypersensitivity] | 4 (50) | 0 | 4 (29)
Hematoma | 2 (25) | 0 | 2 (14)
Increased CSF protein | 1 (13) | 0 | 1 (7)
Pleocytosis | 1 (13) | 0 | 1 (7)
Irritability | 0 | 1 (17) | 1 (7)
Headache | 1 (13) | 0 | 1 (7)
Note: Incidence numbers are based on baseline age group

6.2 Postmarketing Experience

The following adverse reactions have been identified during post-approval use of BRINEURA. Because these reactions are reported voluntarily from a population of uncertain size, it is not always possible to reliably estimate their frequency or establish a causal relationship to drug exposure.

- Immune system disorders: Anaphylactic reaction characterized by acute pyrexia, respiratory distress (bronchospasm, hypoxemia, perioral cyanosis), tachycardia, hypotension, diarrhea, and rash [see Warnings and Precautions (5.1)].
- Infections and infestations: Bacterial meningitis [see Warnings and Precautions (5.2)].

8 USE IN SPECIFIC POPULATIONS

8.1 Pregnancy

Risk Summary

There are no available data on BRINEURA use in pregnant women to inform a drug-associated risk of pregnancy-related outcomes. Animal reproduction studies have not been conducted using cerliponase alfa.

The estimated background risk of major birth defects and miscarriage for the indicated population is unknown. All pregnancies have a background risk of birth defect, loss, or other adverse outcomes. In the U.S. general population, the estimated background risk of major birth defects and miscarriage in clinically recognized pregnancies is 2 to 4% and 15 to 20%, respectively.

8.2 Lactation

Risk Summary

There are no data on the presence of cerliponase alfa in human milk, the effects on the breastfed child, or the effects on milk production. The lack of clinical data during lactation precludes a clear determination of the risk of BRINEURA to an infant during lactation; therefore, the development and health benefits of breastfeeding should be considered along with the mother's clinical need for BRINEURA and any potential adverse effects on the breastfed infant from BRINEURA or from the underlying maternal condition.

8.4 Pediatric Use

The safety and effectiveness of BRINEURA have been established to slow the loss of ambulation in pediatric patients with CLN2 disease and the information on this use is discussed throughout the labeling.

BRINEURA is not recommended for use in patients less than 37 weeks post-menstrual age (gestational age at birth plus post-natal age) or those weighing less than 2.5 kg due to physiologic immaturity which may increase risk of serious and clinically significant adverse reactions observed with BRINEURA [see Warnings and Precautions (5)].

Patients less than 3 years of age may be at increased risk for developing hypersensitivity reactions with BRINEURA use compared to patients 3 years of age and older [see Warnings and Precautions (5.1) and Adverse Reactions (6.1)].

11 DESCRIPTION

Cerliponase alfa is a purified human enzyme produced by recombinant DNA technology in a Chinese hamster ovary cell line. The active substance is a recombinant human tripeptidyl peptidase-1 (rhTPP1), a lysosomal exopeptidase. The primary activity of the mature enzyme is the cleavage of N-terminal tripeptides from a broad range of protein substrates.

Cerliponase alfa contains 544 amino acids with an average molecular mass of 59 kDa. The mature enzyme is 368 amino acids in length. There are 5 consensus N-glycosylation sites on rhTPP1 that contain high mannose, phosphorylated high mannose and complex glycosylation structures.

BRINEURA (cerliponase alfa) Injection and Intraventricular Electrolytes Injection are administered by intraventricular infusion. The solutions are sterile, nonpyrogenic, and free of foreign particulates. BRINEURA is a clear to slightly opalescent and colorless to pale yellow solution. Intraventricular Electrolytes is a clear to colorless solution.

BRINEURA and Intraventricular Electrolytes Injection are packaged in 10 mL clear Type 1 single-dose glass vials [see How Supplied/Storage and Handling (16)]. Each vial of BRINEURA provides 5 mL of solution containing 150 mg cerliponase alfa. Each vial of Intraventricular Electrolytes Injection provides 5 mL of solution. Both BRINEURA and Intraventricular Electrolytes Injection are formulated with the following excipients: calcium chloride dihydrate (1.05 mg); magnesium chloride hexahydrate (0.8 mg); potassium chloride (1.1 mg); sodium chloride (43.85 mg); sodium phosphate, dibasic, heptahydrate (0.55 mg); sodium phosphate, monobasic, monohydrate (0.4 mg); and Water for Injection, USP. The pH of the solution is between 6.2 to 6.8 for BRINEURA, and between 6.0 to 7.0 for Intraventricular Electrolytes Injection.

Each vial contains: sodium: 0.76 mEq, and potassium: 0.015 mEq.

12 CLINICAL PHARMACOLOGY

12.1 Mechanism of Action

CLN2 disease is a neurodegenerative disease caused by deficiency of the lysosomal enzyme tripeptidyl peptidase-1 (TPP1), which catabolizes polypeptides in the CNS. TPP1 has no known substrate specificity. Deficiency in TPP1 activity results in the accumulation of lysosomal storage materials normally metabolized by this enzyme in the central nervous system (CNS), leading to progressive decline in motor function.

Cerliponase alfa (rhTTP1), a proenzyme, is taken up by target cells in the CNS and is translocated to the lysosomes through the Cation Independent Mannose-6-Phosphate Receptor (CI-MPR, also known as M6P/IGF2 receptor). Cerliponase alfa is activated in the lysosome and the activated proteolytic form of rhTPP1 cleaves tripeptides from the N-terminus of proteins.

12.2 Pharmacodynamics

No formal pharmacodynamic studies have been conducted with cerliponase alfa.

12.3 Pharmacokinetics

Patients 3 years of age and older

The pharmacokinetics of cerliponase alfa were evaluated in patients with CLN2 disease who received intraventricular infusions of 30 mg (0.1 times the maximum approved recommended dosage), 100 mg (approximately 0.3 times the maximum approved recommended dosage), and 300 mg over approximately 4.5 hours once every other week.

Cerliponase alfa CSF exposure following the initial single dose administration of BRINEURA increased less than proportionally across doses of 30 mg, 100 mg, and 300 mg. There was no apparent accumulation of cerliponase alfa in CSF or plasma when BRINEURA was administered at a dose of 300 mg once every other week.

Cerliponase alfa pharmacokinetics have high inter-subject and intra-subject variability. Following intraventricular infusions of 300 mg of BRINEURA at Day 1, Week 5, and Week 13, the pharmacokinetic parameters in CSF and plasma were assessed in 14 patients and are summarized in Table 4.

Table 4: Pharmacokinetic Parameters of Cerliponase Alfa Following Intraventricular Infusion (approximately 4.5 hours in duration) of BRINEURA 300 mg Every Two Weeks in Patients ≥ 3 years
 | Parameter | Median [Min, Max]
 | Parameter | Day 1 | Week 5 | Week 13
 | N | 13 | 14 | 13
 | Tmax [Tmax expressed as time since start of ~4.5 hour infusion.] , hr | 4.5 [4.3, 5.8] | 4.3 [3.8, 4.5] | 4.3 [4.0, 4.5]
 | Cmax, mcg/mL | 1260 [359, 4380] | 1630 [376, 4670] | 1390 [1110, 2340]
CSF | AUC0-t, mcg-hr/mL | 9290 [3660, 19000] | 12400 [4620, 26200] | 10500 [7000, 18200]
 | Vss, mL | 245 [78.4, 909] | 196 [85.4, 665] | 186 [131, 257]
 | CL, mL/hr | 32.3 [15.8, 81.9] | 24.2 [11.4, 64.9] | 28.7 [16.5, 42.9]
 | t1/2, hr | 6.2 [5.5, 16.3] | 7.4 [3.3, 9.5] | 7.7 [5.1, 9.4]
 | N | 12 | 12 | 9
Plasma [Vss, CL, and t1/2 were not estimated due to insufficient plasma pharmacokinetic data] | Tmax, hr | 12.0 [4.3, 24.5] | 12.0 [7.5, 24.2] | 12.3 [4.3, 75.9]
 | Cmax, mcg/mL | 1.3 [0.2, 3.9] | 1.9 [0.2, 4.3] | 1.0 [0.03, 2.6]
 | AUC0-t, mcg-hr/mL | 16.2 [1.1, 69.9] | 40.1 [11.1, 78.9] | 9.5 [0.2, 51.6]
 | N | 11 | 12 | 9
CSF/Plasma Ratio | Cmax | 1200 [305, 4530] | 809 [202, 9370] | 1320 [541, 51200]
CSF/Plasma Ratio | AUC0-t | 393 [115, 1910] | 340 [126, 1780] | 1330 [167, 38900]

The estimated CSF volume of distribution of cerliponase alfa following intraventricular infusion of 300 mg of BRINEURA (median Vss = 245 mL) exceeds the typical CSF volume (100 mL).

Pediatric patients less than 3 years

Pediatric CLN2 patients ages 1 to < 2 years (n=2) and 2 to < 3 years (n=6) were administered cerliponase alfa according to the recommended dosing regimen based on age for up to 144 weeks. CSF exposure with 300 mg cerliponase alfa was within the range characterized to be safe and effective in pivotal Trial 1.

Plasma exposure in younger patients trended higher than the range characterized in the pivotal study. The pharmacokinetic parameters summarized by age at time of visit and dose are shown in Table 5.

Table 5: Pharmacokinetic Parameters of Cerliponase Alfa by Age at Visit and Dose Following Intraventricular Infusion of BRINEURA Every Two Weeks in Pediatric Patients < 3 years
Age at Visit | Dose (mg) |  | Parameter | Median [Min, Max]
1 to < 2 years | 200 | CSF | N | 3
1 to < 2 years |  |  | Cmax, mcg/mL | 511 [163, 987]
 |  |  | AUC0-t, mcg-hr/mL | 2720 [1100, 5050]
 |  | Plasma | N | 2
 |  |  | Cmax, mcg/mL | 10.4 [9.46, 11.3]
 |  |  | AUC0-t, mcg-hr/mL | 91.8 [72.7, 111]
 | 300 | CSF | N | 2
 |  |  | Cmax, mcg/mL | 566 [496, 636]
 |  |  | AUC0-t, mcg-hr/mL | 8030 [8030, 8030] [N=1 due to less than 3 evaluable datapoints for determination of AUC0-t]
 |  | Plasma | N | 2
 |  |  | Cmax, mcg/mL | 14.1 [11.2, 17.0]
 |  |  | AUC0-t, mcg-hr/mL | 145 [82.7, 206]
2 to < 3 years | 300 | CSF | N | 6
2 to < 3 years |  |  | Cmax, mcg/mL | 896 [508, 1790]
 |  |  | AUC0-t, mcg-hr/mL | 4100 [2380, 6720] [N=5 due to less than 3 evaluable datapoints for determination of AUC0-t]
 |  | Plasma | N | 6
 |  |  | Cmax, mcg/mL | 14.9 [9.08, 35.3]
 |  |  | AUC0-t, mcg-hr/mL | 163 [91.5, 320]

Cerliponase alfa is a protein and is expected to be degraded through peptide hydrolysis.

12.6 Immunogenicity

The observed incidence of anti-drug antibodies is highly dependent on the sensitivity and specificity of the assay. Differences in assay methods preclude meaningful comparisons of the incidence of anti-drug antibodies in the studies described below with the incidence of anti-drug antibodies in other studies including cerliponase alfa.

In Trials 1 and 2 [see Clinical Studies (14)], 19 of 24 (79%) and 10 of 24 (42%) patients treated with BRINEURA developed anti-drug antibodies (ADAs) in serum and CSF, respectively. Drug-specific neutralizing antibodies (NAb) capable of inhibiting receptor-mediated cellular uptake of cerliponase alfa were detected in the CSF of 3 of 24 (13%) patients at a single visit and were undetectable in all other CSF samples tested in ADA positive patients. In Trial 3 [see Clinical Studies (14)], 14 of 14 (100%) and 3 of 14 (21%, all of the 3 patients were < 3 years of age) patients treated with BRINEURA developed ADAs in serum and CSF, respectively. NAb responses were not detected in the CSF of any ADA positive patients. Overall, patients younger than 3 years of age had higher ADA titers compared to patients 3 years of age and older.

In Trials 1 and 2, patients who experienced moderate to severe hypersensitivity adverse reactions were tested for drug-specific IgE and found to be negative. No association was found between serum ADA titers and incidence or severity of hypersensitivity. In Trial 3, hypersensitivity occurred in higher percentage in BRINEURA-treated patients < 3 years of age at baseline (amongst these patients, one patient experienced anaphylaxis), and higher ADA titers were also observed in this age group compared to patients ≥ 3 years of age at baseline. There was no identified clinically significant effect of ADA on pharmacokinetics or efficacy of BRINEURA. There is insufficient information to characterize the effects of ADA on safety.

13 NONCLINICAL TOXICOLOGY

13.1 Carcinogenesis, Mutagenesis, Impairment of Fertility

Carcinogenicity, genotoxicity, and fertility studies have not been performed with cerliponase alfa. Based on the mechanism of action, cerliponase alfa is not expected to be tumorigenic.

14 CLINICAL STUDIES

The efficacy of BRINEURA was assessed over 96 weeks in a non-randomized single-arm dose escalation clinical study with extension in symptomatic pediatric patients with late infantile neuronal ceroid lipofuscinosis type 2 (CLN2) disease, confirmed by TPP1 deficiency. BRINEURA-treated patients were compared to untreated patients from a natural history cohort. The Motor domain of a CLN2 Clinical Rating Scale was used to assess disease progression. Scores ranged from 3 (grossly normal) to 0 (profoundly impaired) with unit decrements representing milestone events in the loss of motor function (ability to walk or crawl). Due to the inability to establish comparability for the CLN2 Language domain ratings between the clinical study with extension and the natural history cohort, efficacy of BRINEURA for the Language domain cannot be established.

Twenty-four patients, aged 3 to 8 years were enrolled in the BRINEURA single-arm clinical study (Trial 1, NCT01907087). Sixty-three percent of patients were female and 37% were male. Ninety-six percent of patients were White and 4% were Asian; for ethnicity, 4% identified as Hispanic/Latino, 96% as non-Hispanic/Latino. One patient withdrew after week 1 due to inability to continue with study procedures; 23 patients were treated with BRINEURA 300 mg every other week by intraventricular infusion for 48 weeks, and continued treatment during the 240-week extension period, Trial 2 (NCT02485899), for a total duration of 288 weeks, plus a 24-week safety follow-up.

In the clinical study with extension, patients were assessed for decline in the Motor domain of the CLN2 Clinical Rating Scale at 48, 72 and 96 weeks. Decline was defined as having an unreversed (sustained) 2-category decline or an unreversed score of 0 in the Motor domain of the CLN2 Clinical Rating Scale. Patients' responses to BRINEURA treatment were evaluated if at screening a combined Motor plus Language CLN2 score of less than 6 was recorded. Two patients with a combined Motor plus Language CLN2 score of 6 were excluded from the analyses; they maintained that score throughout the study period. The patient who terminated early was analyzed as having a decline at the time of termination. Data used in the analyses from the natural history cohort began at 36 months of age or greater and at the first time a Motor plus Language CLN2 score less than 6 was recorded.

Motor scores of the 22 BRINEURA-treated patients in the clinical study with extension were compared to scores of the independent natural history cohort that included 42 untreated patients who satisfied inclusion criteria for the clinical study. The results of logistic modeling with covariates (screening age, screening motor score, genotype: 0 key mutations (yes/no)), demonstrated the odds of BRINEURA-treated patients not having a decline by 96 weeks were 13 times the odds of natural history cohort patients not having a decline (Odds Ratio (95% CI): 13.1 (1.2, 146.9)).

Descriptive non-randomized comparison

In an unadjusted non-randomized comparison, of the 22 patients treated with BRINEURA and evaluated for efficacy at week 96, 21 (95%) did not decline, and only the patient who terminated early was deemed to have a decline in the Motor domain of the CLN2 Clinical Rating Scale. Results from the natural history cohort demonstrated progressive decline in motor function; of the 42 patients in the natural history cohort, 21 (50%) experienced an unreversed (sustained) 2-category decline or unreversed score of 0 in the Motor domain of the CLN2 Clinical Rating Scale over 96 weeks.

Given the non-randomized study design, a Cox Proportional Hazards Model adjusted for age, initial motor score, and genotype was used to evaluate time to unreversed 2-category decline or unreversed score of 0 in the Motor domain. This model showed a lesser decrease in motor function in the BRINEURA-treated patients when compared to the natural history cohort (see Figure 7).

Figure 7. Estimated Time to Unreversed (Sustained) 2-Category Decline or Unreversed Score of Zero in Motor Domain for Symptomatic Pediatric Patients in the BRINEURA Trials 1 and 2 at 96 Weeks and for Patients in a Natural History Cohort (Based on the Cox Proportional Hazards Model Adjusting for Covariates)

Shading represents 95% confidence intervals.
Follow-up for the natural history cohort begins at 36 months of age or greater and at the first time a Motor plus Language CLN2 score less than 6 was recorded.
The BRINEURA-treated population is the full population (N=24) minus two patients with baseline Motor plus Language CLN2 score = 6.
Covariates: screening age, screening Motor score, genotype: 0 key mutations (yes/no). "Screening age" was defined in the natural history cohort as the age at the first time a Motor plus Language CLN2 score less than 6 was recorded, and no earlier than 36 months of age. The "screening Motor score" of the natural history cohort was defined as the Motor score at the screening age.
Decline is defined as an unreversed (sustained) 2-category decline or unreversed score of 0 in the Motor domain of the CLN2 Clinical Rating Scale.

Motor Domain Scores: Matched Patients Only

To further assess efficacy, the 22 patients from the BRINEURA clinical study with a baseline combined Motor plus Language CLN2 score less than 6 were matched to 42 patients in the natural history cohort. Patients were matched based on the following covariates: baseline age at time of screening within 3 months, genotype (0, 1, or 2 key mutations), and baseline Motor domain CLN2 score at time of screening.

Using the Motor domain of the CLN2 Clinical Rating Scale, decline was defined as having an unreversed 2-category decline or an unreversed score of 0. At 96 weeks, the matched analysis based on 17 pairs demonstrated fewer declines in the Motor domain for BRINEURA-treated patients compared to untreated patients in the natural history cohort (see Table 6).

Table 6: Proportion of Matched Symptomatic Pediatric Patients with CLN2 Disease without Decline [Decline is defined as an unreversed (sustained) 2-category decline or unreversed score of 0 in the Motor domain of the CLN2 Clinical Rating Scale.] in the BRINEURA Trials 1 and 2 and in the Natural History Cohort assessed at Weeks 48, 72, and 96
Time Point/Period | Natural History Cohort (N=17) | BRINEURA-Treated (N=17) | Difference | Odds Ratio [Based on McNemar's Exact test]
Time Point/Period | n (%) | n (%) | % (95% CI [Exact confidence interval for risk difference (Santner and Snell)]) | OR (95% CI)
Follow-up through Week 48 | 13 (76) | 16 (94) | 18% (-19, 51) | 4 (0.4, 200)
Follow-up through Week 72 | 11 (65) | 16 (94) | 29% (-7, 61) | 5.9 (0.7, 250)
Follow-up through Week 96 | 6 (35) | 16 (94) | 59% (24, 83) | 11 (1.6, 500)
Matched on baseline age at time of screening within 3 months, genotype (0, 1, or 2 key mutations), and baseline Motor domain CLN2 score at time of screening.
The BRINEURA-treated population is based on the full population minus two patients with baseline Motor plus Language CLN2 score = 6.

Trial 3 (NCT02678689) was a Phase 2, open label clinical study designed to enroll symptomatic and presymptomatic CLN2 patients less than 18 years of age. The trial enrolled 14 patients ranging in age from 1 to 6 years at baseline, including 8 patients less than 3 years of age, the median age was 2.7 years. Patients received BRINEURA at the recommended dose every 2 weeks by intraventricular infusion for 144 weeks (1 patient withdrew to receive treatment commercially). Fifty-seven percent of patients were female and 43% were male. All patients were White; for ethnicity, 14% identified as Hispanic/Latino, 86% as non-Hispanic/Latino. The mean baseline CLN2 Motor score was 2.3 (standard deviation (SD) 0.83) with a range from 1 to 3.

Thirteen of the 14 BRINEURA treated patients were matched with up to 3 natural history comparators on the basis of age within 3 months, equal CLN2 Motor score, and genotype (0, 1, or 2 key mutations). None of the BRINEURA treated patients (N=14) had a 2-point decline or score of zero in the Motor scale by Week 169. Among the matched natural history comparators (N=31), 20 subjects (65%) had an unreversed 2-point decline or score of zero by last assessment.

The median time to an unreversed 2-point decline in Motor score or score of 0 was 133 weeks among the natural history comparators and was not reached by last assessment (Week 169) in patients treated with BRINEURA.

In patients below 3 years of age, none (0%) of the BRINEURA treated patients (N=8) had a 2-point decline or score of zero in the Motor score by Week 169. Among the 8 treated patients, 7 were matched to 18 untreated patients from the natural history cohort. Among the matched natural history comparators (N=18), 11 subjects (61%) had an unreversed 2-point decline or score of zero in the Motor score by last assessment. All seven of the treated patients below 3 years of age with a motor score of 3 at baseline remained at a motor score of 3 at the last measured timepoint, which represents grossly normal gait. In this population BRINEURA treated patients showed a delay in disease onset.

16 HOW SUPPLIED/STORAGE AND HANDLING

BRINEURA is supplied as a sterile, clear to slightly opalescent and colorless to pale yellow solution for intraventricular infusion and Intraventricular Electrolytes Injection is supplied as a clear to colorless solution for intraventricular infusion; both are included in package 1 of 2. The Administration Kit for use with BRINEURA is supplied separately as package 2 of 2 [see Dosage and Administration (2.4)].

Package 1 of 2

Each BRINEURA (cerliponase alfa) Injection vial has a green flip-off cap (plastic) and contains 150 mg cerliponase alfa per 5 mL (30 mg/mL).

Each Intraventricular Electrolytes Injection vial has a yellow flip-off cap (plastic) and contains 5 mL of solution.

Contents of Package 1 | NDC Number
BRINEURA (cerliponase alfa) Injection (2 vials of 150 mg/5 mL) Intraventricular Electrolytes Injection (1 vial, 5 mL) | 68135-811-02

Package 2 of 2

The Administration Kit for use with BRINEURA is supplied separately and contains the following single-use, sterile infusion components:

- Two 20-mL syringes
- Two syringe needles (21 G, 25.4 mm)
- One extension line
- One infusion set with 0.2 micron inline filter
- One port needle (22 G, 16 mm)

Storage

BRINEURA (cerliponase alfa) Injection and Intraventricular Electrolytes Injection:
Store upright in a freezer (-25°C to -15°C) in original carton to protect from light.

Administration Kit for use with BRINEURA:
Store in original carton separately from BRINEURA. Do not freeze.

17 PATIENT COUNSELING INFORMATION

- Hypersensitivity Reactions Including Anaphylaxis and Infusion-Associated Reactions (IARs)
  - Advise patients and caregivers that life-threatening hypersensitivity reactions, including anaphylaxis, and IARs may occur with BRINEURA treatment.
  - Advise patients and caregivers that anaphylaxis has occurred during the early course of enzyme replacement therapy and after extended duration of therapy.
  - Inform patients and caregivers of the symptoms of life-threatening hypersensitivity reactions, including anaphylaxis, and IARs and to seek immediate medical care should symptoms occur [see Warnings and Precautions (5.1, 5.5)].
- Intraventricular Access Device-Related Infections
  Advise patients and caregivers of the risk of device-related infections, including meningitis. Familiarize them with the signs and symptoms of these infections and instruct them to immediately contact their healthcare provider if an infection is suspected [see Warnings and Precautions (5.2)].
- Cardiovascular Adverse Reactions
  Advise patients and caregivers that hypotension and/or bradycardia may occur during and following the infusion of BRINEURA. Instruct patients immediately to contact their healthcare provider if these reactions occur [see Warnings and Precautions (5.4)].

Manufactured by:
BioMarin Pharmaceutical Inc.
Novato, CA 94949
US License Number 1649
1-866-906-6100 (phone)

Codman® and the B Braun Perfusor® are the registered trademarks of their respective owners and are not trademarks of BioMarin® Pharmaceutical Inc.

PRINCIPAL DISPLAY PANEL - Kit Carton - Package 1

NDC 68135-811-02

Brineura®
(cerliponase alfa)
Injection

150 mg/5 mL (30 mg/mL)

For Intraventricular Infusion Only

Each vial of Brineura® contains 150 mg cerliponase alfa
in 5 mL of solution (30 mg/mL)

No preservatives
Single-Dose Vial. Discard unused portion.

Brineura® and Intraventricular Electrolytes must be
administered with the Administration Kit provided.

Each carton contains:
2 vials, each containing Brineura®
(cerliponase alfa) Injection, 150 mg/5 mL
1 vial of Intraventricular Electrolytes
Injection, 5 mL

Package 1 of 2

Administration Kit is supplied
and stored separately as
package 2 of 2.

Rx Only

BIOMARIN®

PRINCIPAL DISPLAY PANEL - 150 mg/5 mL Vial Label

Brineura®
(cerliponase alfa)
Injection

150 mg/5 mL
(30 mg/mL)

For Intraventricular Infusion Only
Use before Intraventricular
Electrolytes

PRINCIPAL DISPLAY PANEL - 5 mL Vial Label

Intraventricular
Electrolytes

Injection

Use after Brineura®
(cerliponase alfa)

5 mL

For Intraventricular
Infusion Only

PRINCIPAL DISPLAY PANEL - Kit Carton - Package 2

Administration Kit for use with Brineura® (cerliponase alfa)
Intraventricular infusion only

Recommended Dosage: See Prescribing Information

Contents of Administration Kit:

- Two single-use 20-mL syringes
- Two single-use syringe needles, 21 G, 25.4 mm
- One single-use extension line
- One single-use infusion set with 0.2 micron inline filter
- One single-use port needle, 22 G, 16 mm

Package 2 of 2

Brineura® and Intraventricular Electrolytes Injection are separately supplied and
stored frozen as package 1 of 2
Not for resale
Only for use with Brineura®

Caution:

- Do not use if the seals or package are damaged.
- Do not resterilize.
- Single use only. Do not reuse.
- Do not freeze.
- Store in original package separately from Brineura®.

NOTE:

- This Administration Kit has no components made of natural latex rubber.
- Individual devices are provided in separate sterile packaging.
- Expiration dates may vary for each device included.

Manufactured for
BioMarin Pharmaceutical Inc.
Novato, CA 94949
www.bmrn.com

Rx Only

BIOMARIN®